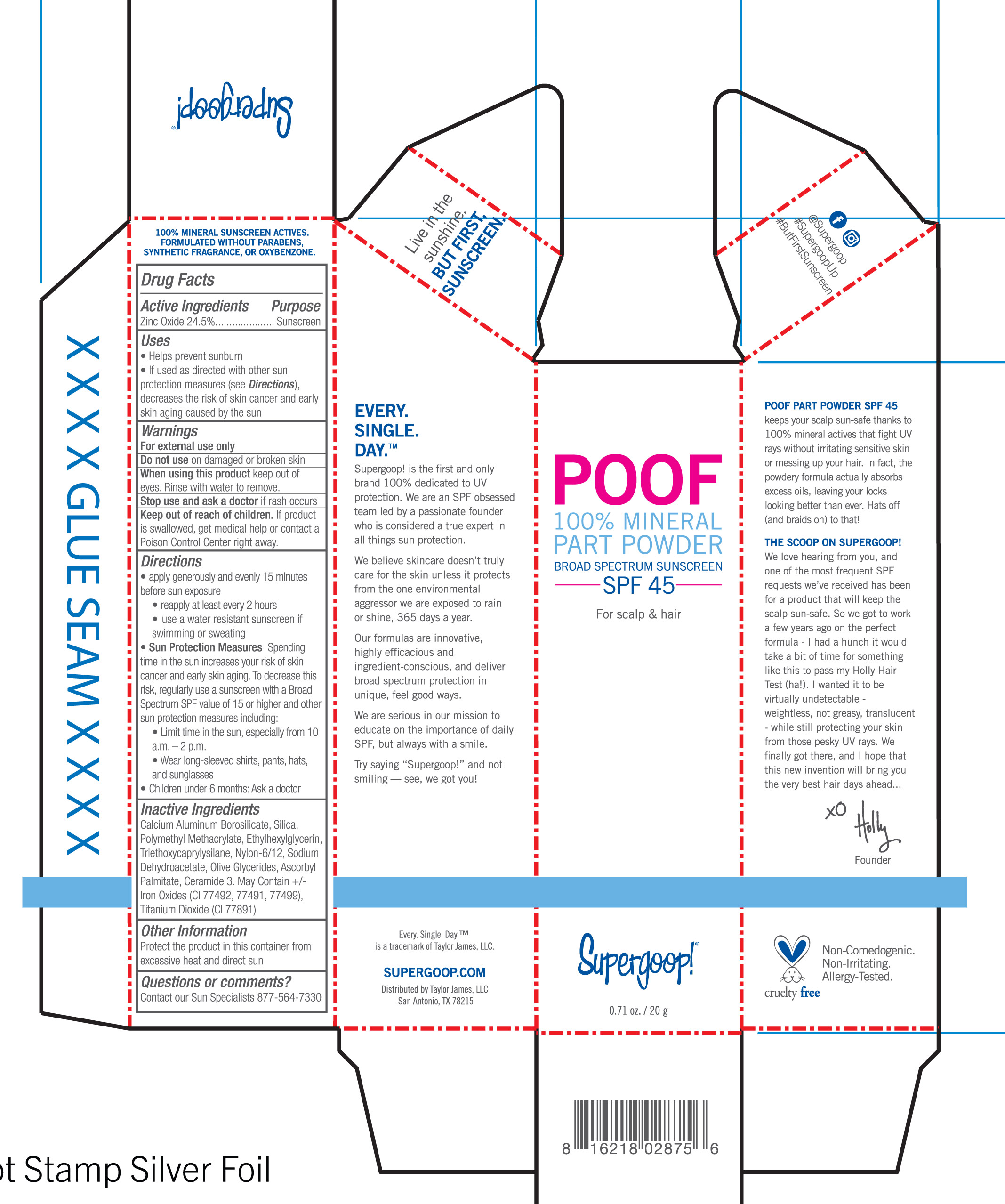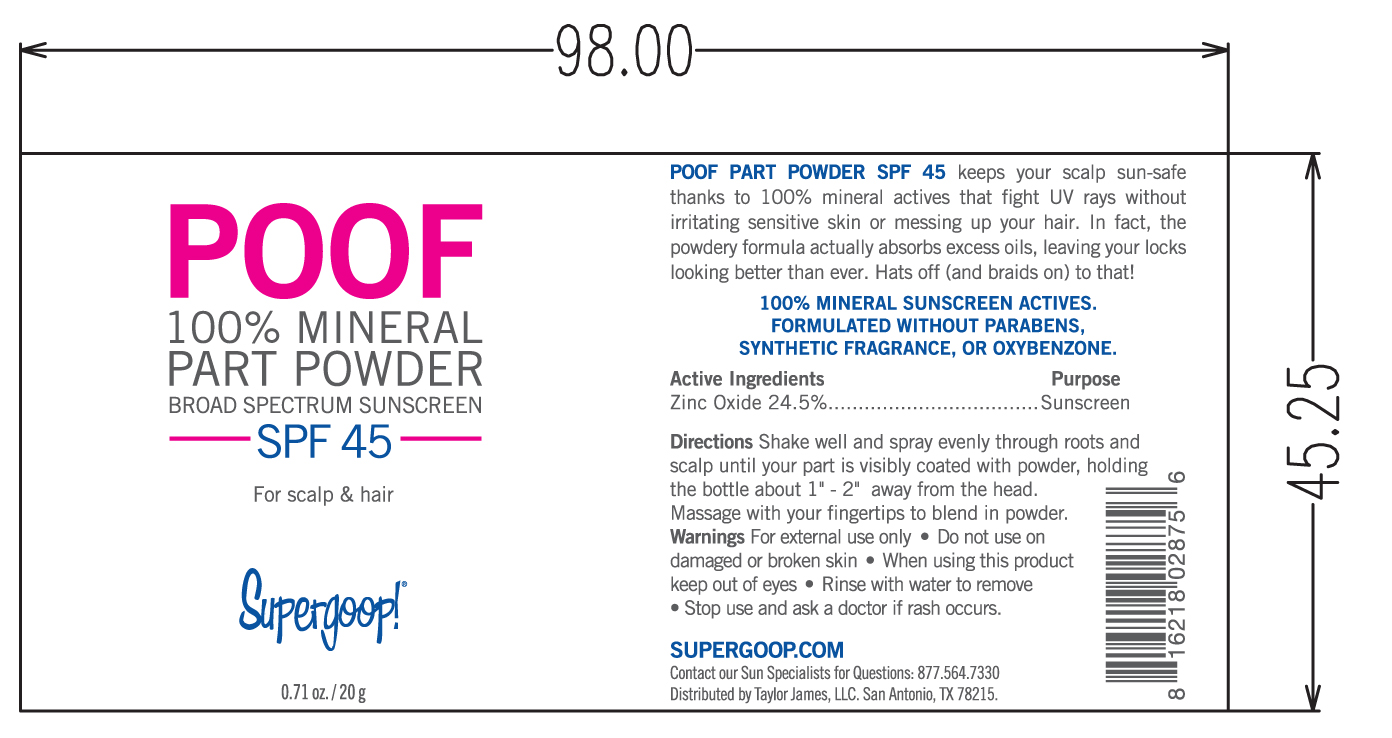 DRUG LABEL: Poof 100% Mineral Part Broad Spectrum Sunscreen SPF 45
NDC: 75936-300 | Form: POWDER
Manufacturer: TAYLOR JAMES, LTD
Category: otc | Type: HUMAN OTC DRUG LABEL
Date: 20190123

ACTIVE INGREDIENTS: ZINC OXIDE 24.5 g/100 g
INACTIVE INGREDIENTS: FERROSOFERRIC OXIDE; FERRIC OXIDE YELLOW; SILICON DIOXIDE; SODIUM DEHYDROACETATE; TRIETHOXYCAPRYLYLSILANE; TITANIUM DIOXIDE; ASCORBYL PALMITATE; CERAMIDE NP; FERRIC OXIDE RED; CALCIUM ALUMINUM BOROSILICATE; POLY(METHYL METHACRYLATE; 450000 MW); ETHYLHEXYLGLYCERIN

Poof 100% Mineral Part Powder Broad Spectrum Sunscreen SPF 45

Active Ingredients Purpose

Zinc Oxide 24.5% Sunscreen

Uses

- Helps Prevent Sunburn
- If used as directed with other sun protection measures (see Directions), decreases the risk of skin cancer and early skin aging caused by the sun

Keep out of reach of children. If product is swallowed, get medical help or contact a poison control center right away.

Stop use and ask a doctor if rash occurs.

Warnings

For external use only

Do not use on damaged or broken skin

When using this product keep out of eyes. Rinse with water to remove.

Directions

- Apply generously and evenly 15 minutes before sun exposure
- reapply at least every 2 hours
- use a water resistant sunscreen if swimming or sweating
- Sun Protection Measures Spending time in the sun increases your risk of skin cancer and early skin aging. To decrease this risk, regularly use a sunscreen with a Broad Spectrum value of 15 or higher and other sun protection measures including:
- Limit time in the sun ftom 10 a.m. - 2 p.m.
- wear long-sleeved shirts, pants, hats, and sunglasses
- Children under 6 months: Ask a doctor

INACTIVE INGREDIENT

Calcium Aluminum Borosilicate, Silica, Polymethyl Methacrylate, Ethylglycerin, Triethanolamine, Nylon-6/12, Sodium Dehydroacetate, Olive Glycerides, Ascorbyl palmitate, Ceramide-3.May Contain+/- Iron Oxides(CI 77492, CI 77491, 77499), Titanium Dioxide (CI 77891)

PACKAGE LABEL

Poof 100% mineral part Powder

Broad Spectrum Sunscreen SPF 45

For Scalp and hair

0.71 oz, 20 g